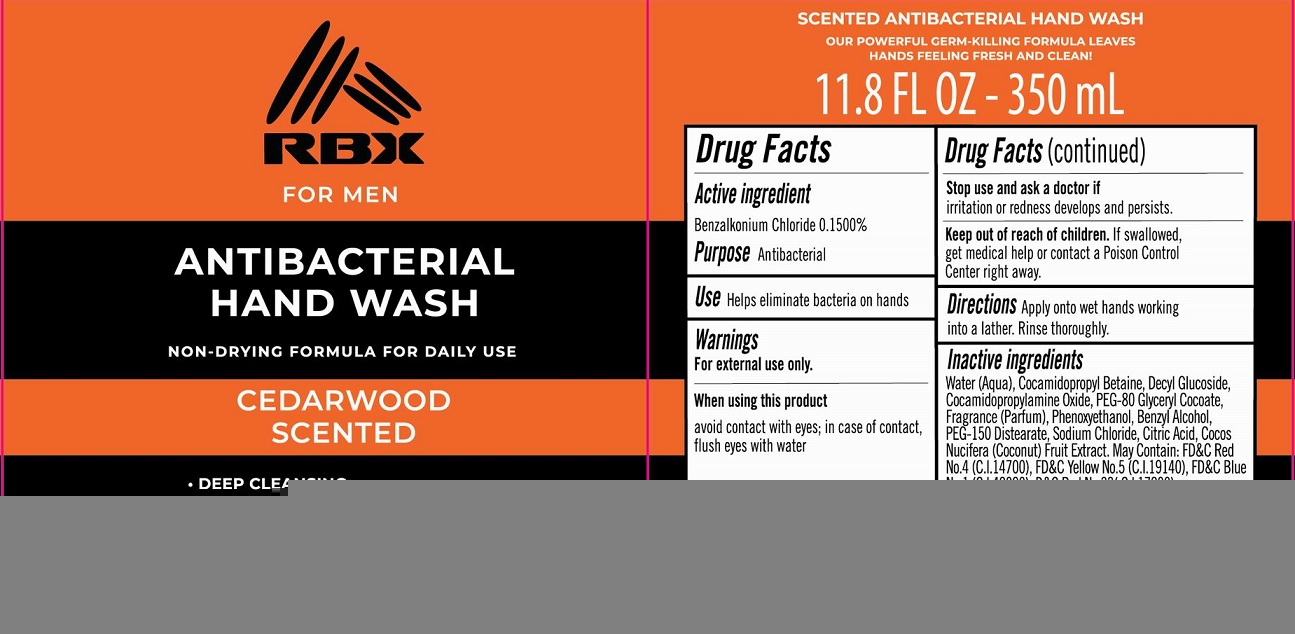 DRUG LABEL: RBX For Men Antibacterial Hand Wash Cedarwood Scented
NDC: 56136-502 | Form: LIQUID
Manufacturer: Ganzhou Olivee Cosmetic Co., Ltd.
Category: otc | Type: HUMAN OTC DRUG LABEL
Date: 20201116

ACTIVE INGREDIENTS: BENZALKONIUM CHLORIDE 1.5 mg/1 mL
INACTIVE INGREDIENTS: WATER; COCAMIDOPROPYL BETAINE; COCAMIDOPROPYLAMINE OXIDE; BENZYL ALCOHOL; GLYCERIN; ACETYLTRIETHYL CITRATE; PHENOXYETHANOL; .ALPHA.-TOCOPHEROL ACETATE, D-; COCONUT OIL; FD&C RED NO. 3; FD&C RED NO. 4; FD&C YELLOW NO. 5; FD&C BLUE NO. 1; D&C RED NO. 33

Active ingredient

Benzalkonium Chloride 0.15%

Purpose

Antibacterial

Use

Helps eliminate bacteria on hands

Warnings

For external use only.

When using this product

avoid contact with eyes; in case of contact, flush eyes with water.

Stop use and ask a doctor if

- irritation and redness develops and persists.

Keep out of reach of children.

If swallowed, get medical help or contact a Poison Control Center right away.

Directions

Apply onto wet hands working into a lather. Rinse thorougly.

Inactive ingredients

Water (Aqua), Cocamidopropyl Betaine, Cocamidopropylamine Oxide, Hydroxethylcellulose, Fragrance (Parfum), Phenoxyethanol, Bezyl Alcohol, PEG-150 Distearate, Sodium Chloride, Glycerin, Citric Acid, Tocopheryl Acetate, Cocos Nucifera (Coconut) Fruit. May contain: FD&C Red No. 4 (C.I. 14700), FD&C Yellow No. 5 (C.I. 19140), D&C Red No. 33 (Cl 17200), FD&C Blue No. 1 (Cl 42090).